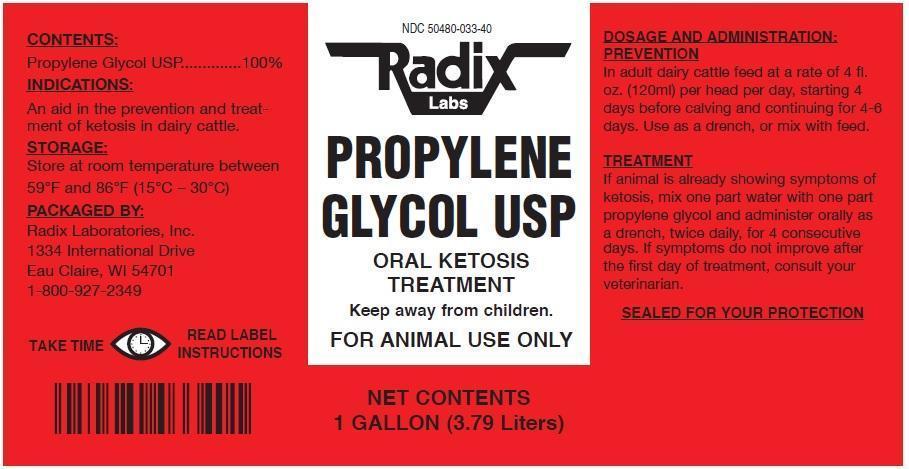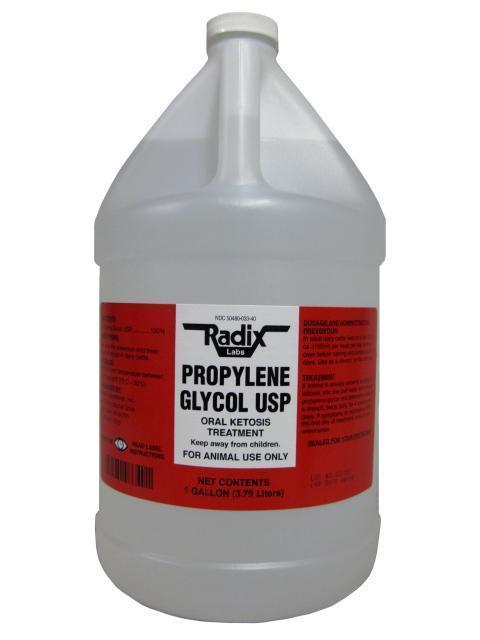 DRUG LABEL: Propylene Glycol
NDC: 50480-033 | Form: LIQUID
Manufacturer: Radix Laboratories, Inc.
Category: animal | Type: OTC ANIMAL DRUG LABEL
Date: 20141219

ACTIVE INGREDIENTS: PROPYLENE GLYCOL 1.036 g/1 mL

Propylene Glycol

• Contents:

- Propylene Glycol USP......................100%

INDICATIONS:

- An aid in the prevention and treatment of ketosis in dairy cattle.

Storage:

- Store at controlled room temperature between 59oF to 86oF (15oC -30oC).

Warning:

- SEALED FOR YOUR PROTECTION
- FOR ANIMAL USE ONLY

Dosage and administration:

- In adult dairy cattle, feed at a rate of 4 fl. oz. (120ml) per head per day, starting 4 days before calving and continuing for 4-6 days. use as a drench, or mix with feed.

- Keep away from children.